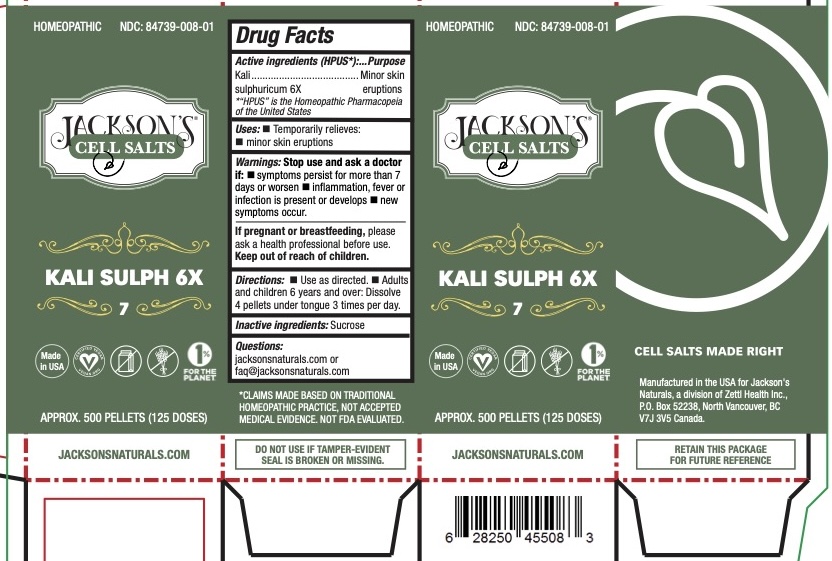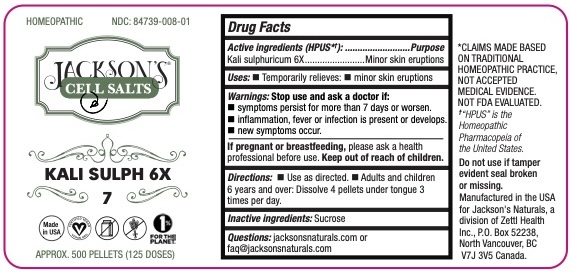 DRUG LABEL: Jacksons Cell Salts KALI SULPH 6X
NDC: 84739-008 | Form: PELLET
Manufacturer: Zettl Health Inc.
Category: homeopathic | Type: HUMAN OTC DRUG LABEL
Date: 20250603

ACTIVE INGREDIENTS: POTASSIUM SULFATE 6 [hp_X]/6 [hp_X]
INACTIVE INGREDIENTS: SUCROSE

Jacksons Cell Salts KALI SULPH 6X

Active Ingredients

Kali sulphuricum 6X

Purpose

Kali sulphuricum -- Minor skin eruptions

Uses

Temporarily relieves:

• minor skin eruptions

Warnings

Stop use and ask a doctor if:

- symptoms persist for more than 72 hours or worsen
- new symptoms occur

If pregnant or breast-feeding ask a health professional before use

Keep out of reach of children

*The letters “HPUS” indicate that these ingredients are officially monographed in the Homeopathic Pharmacopeia of the United States

*CLAIMS BASED ON TRADITIONAL HOMEOPATHIC PRACTICE NOT ACCEPTED MEDICAL EVIDENCE. NOT FDA EVALUATED.

DO NOT USE IF TAMPER-EVIDENT SEAL IS BROKEN OR MISSING.

JACKSONSNATURALS.COM

Inactive Ingredients

sucrose

Directions

- Use as directed.
- Adults and children 6 years and over: Dissolve 4 pellets under tongue 1-3 times per day.

Questions:

jacksonsnaturals.com or

faq@jacksonsnaturals.com